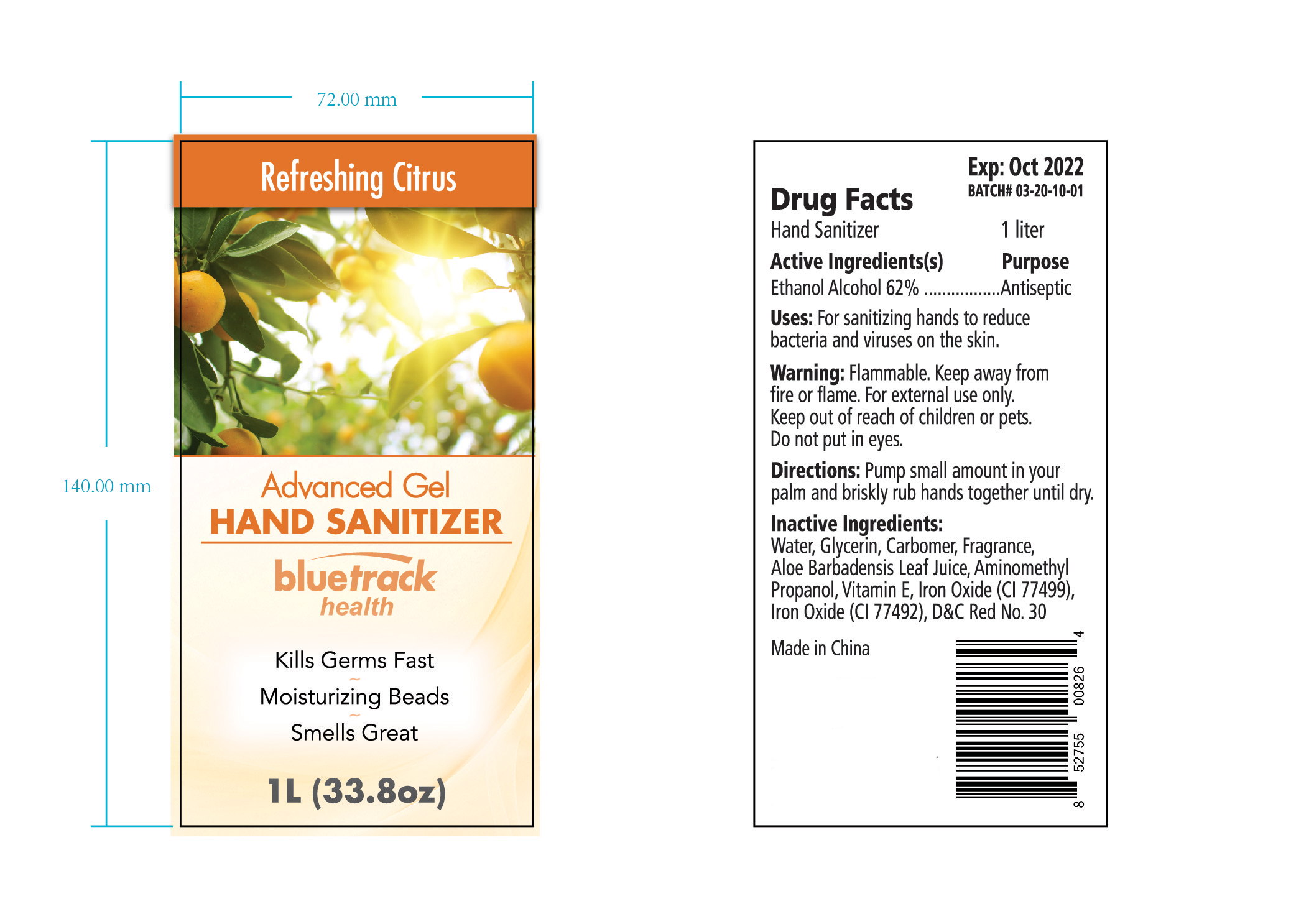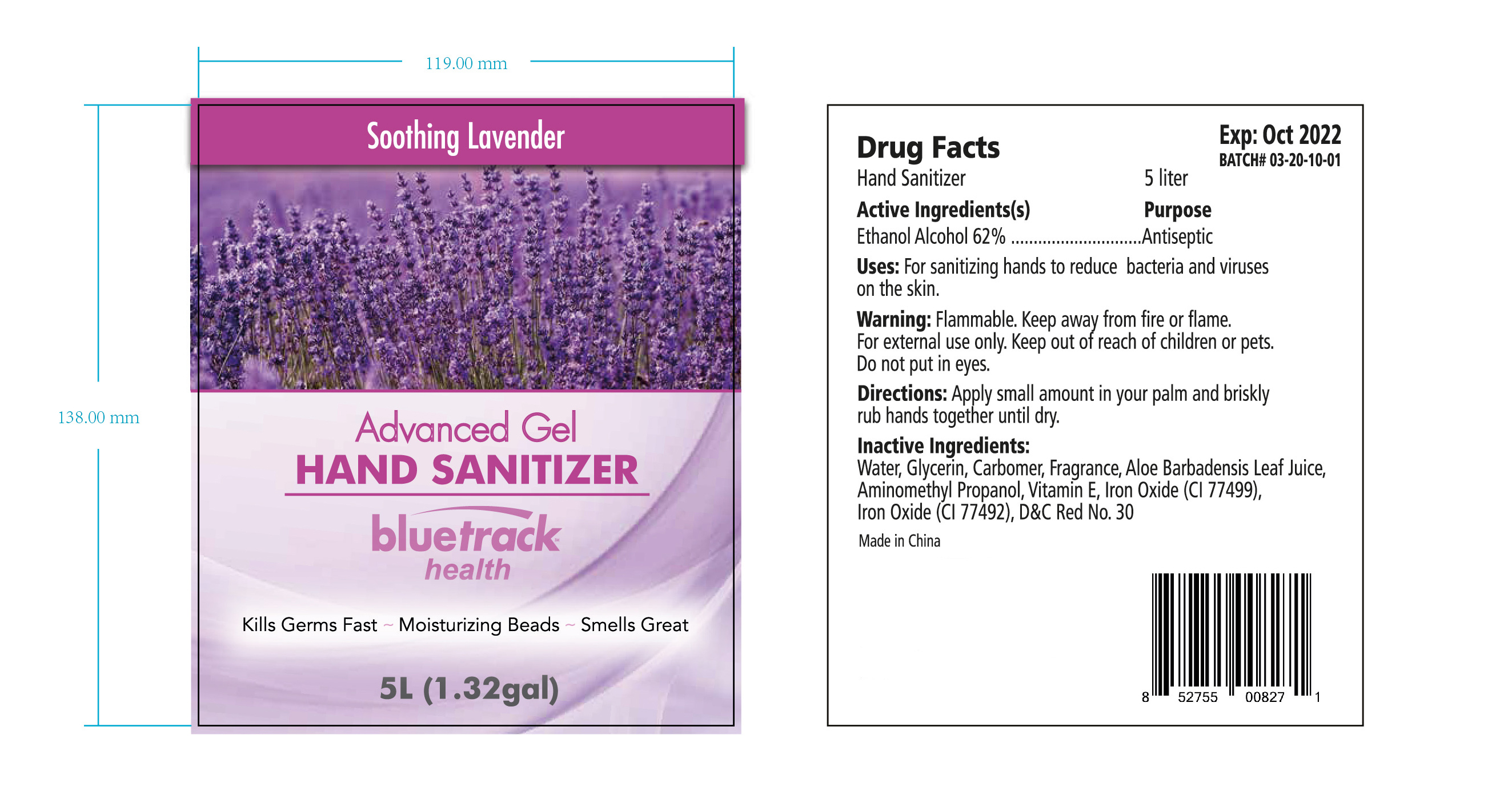 DRUG LABEL: HAND SANITIZER
NDC: 47993-320 | Form: GEL
Manufacturer: NINGBO JIANGBEI OCEAN STAR TRADING CO.,LTD
Category: otc | Type: HUMAN OTC DRUG LABEL
Date: 20201103

ACTIVE INGREDIENTS: ALCOHOL 62 g/112 mL
INACTIVE INGREDIENTS: WATER; GLYCERIN; CARBOMER 940; ALOE VERA LEAF; AMINOMETHYLPROPANOL; TOCOPHEROL; FERROSOFERRIC OXIDE; FERRIC OXIDE YELLOW; D&C RED NO. 30

47993-320

Active Ingredients

Ethyl alcohol 62%

PURPOSE

Antiseptic

Uses：

For sanitizing hands to reduce bacteria and viruses on the skin.

Warnings:

Flammable. Keep away from fire and flame.

For external use only.

Keep out of reach of children or pets.

WHEN USING

Do not put in eyes.

Stop use and ask a doctor if irritation or rash appears and lasts.

Directions:

Apply small amount in your palm and briskly rub hands together until dry.

Inactive Ingredients:

Water, Glycerin, Carbomer, Fragrance, Aloe Barbadensis Leaf Juice, Aminomethyl Propanol, Vitamin E, Iron Oxide(CI 77499),

Iron Oxide(CI 77492), D&C Red No.30.